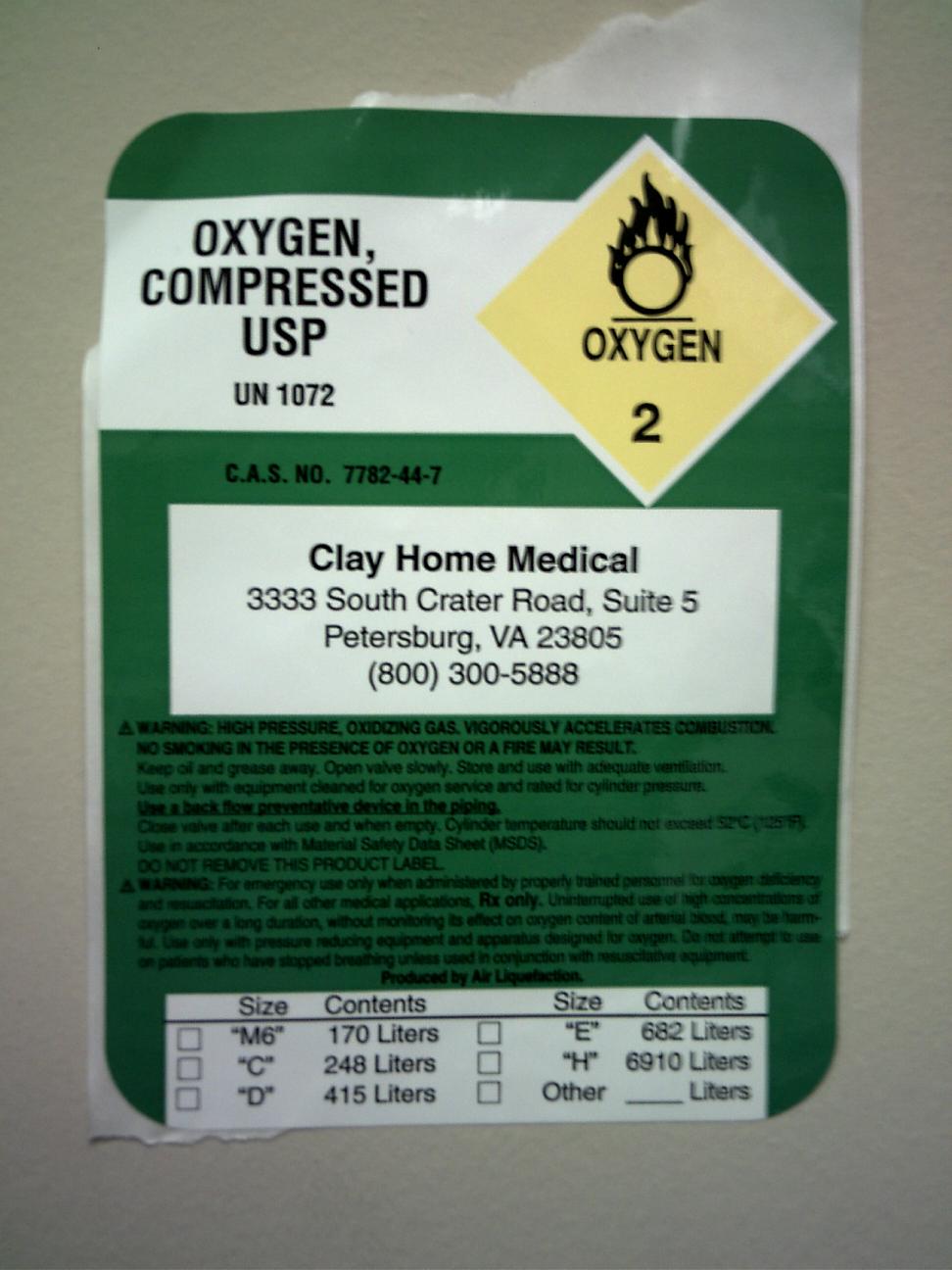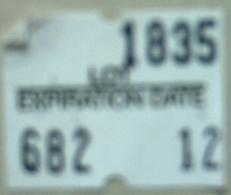 DRUG LABEL: Oxygen
NDC: 65703-5044 | Form: GAS
Manufacturer: Complete Care Medical Inc.
Category: prescription | Type: HUMAN PRESCRIPTION DRUG LABEL
Date: 20100112

ACTIVE INGREDIENTS: Oxygen 99 L/100 L

Oxygen